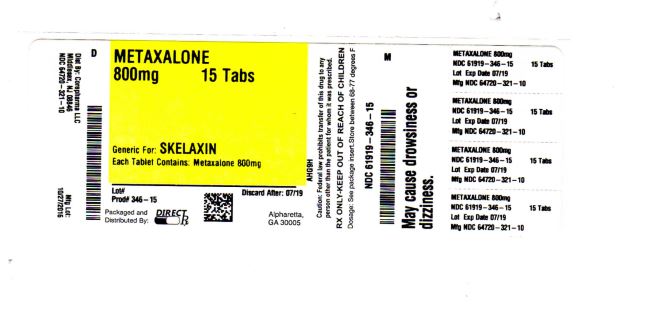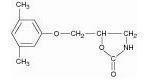 DRUG LABEL: METAXALONE
NDC: 61919-346 | Form: TABLET
Manufacturer: DIRECT RX
Category: prescription | Type: HUMAN PRESCRIPTION DRUG LABEL
Date: 20200120

ACTIVE INGREDIENTS: METAXALONE 800 mg/1 1
INACTIVE INGREDIENTS: ALGINIC ACID; MAGNESIUM STEARATE; STARCH, CORN; CALCIUM ALGINATE

METAXALONE

DESCRIPTION SECTION

Metaxalone tablets are available as an 800 mg oval, convex pink tablet.

Chemically, metaxalone is 5-[(3,5- dimethylphenoxy) methyl]-2-oxazolidinone. The empirical formula is C12H15NO3, which corresponds to a molecular weight of 221.25. The structural formula is:

Metaxalone is a white to almost white, odorless crystalline powder freely soluble in chloroform, soluble in methanol and in 96% ethanol, but practically insoluble in ether or water.

Each tablet contains 800 mg metaxalone and the following inactive ingredients: alginic acid, ammonium calcium alginate, B-Rose Liquid, corn starch and magnesium stearate

CLINICAL PHARMACOLOGY SECTION

Mechanism of Action

The mechanism of action of metaxalone in humans has not been established, but may be due to general central nervous system depression. Metaxalone has no direct action on the contractile mechanism of striated muscle, the motor end plate or the nerve fiber.

Pharmacokinetics

The pharmacokinetics of metaxalone have been evaluated in healthy adult volunteers after single dose administration of metaxalone tablets under fasted and fed conditions at doses ranging from 400 mg to 800 mg.

Absorption

Peak plasma concentrations of metaxalone occur approximately 3 hours after a 400 mg oral dose under fasted conditions. Thereafter, metaxalone concentrations decline log-linearly with a terminal half-life of 9.0 ± 4.8 hours. Doubling the dose of metaxalone tablets from 400 mg to 800 mg results in a roughly proportional increase in metaxalone exposure as indicated by peak plasma concentrations (Cmax) and area under the curve (AUC). Dose proportionality at doses above 800 mg has not been studied. The absolute bioavailability of metaxalone is not known.

The single-dose pharmacokinetic parameters of metaxalone in two groups of healthy volunteers are shown in Table 1.

Table 1: Mean (%CV) Metaxalone Pharmacokinetic Parameters
Dose (mg) | Cmax (ng/mL) | Tmax (h) | AUC∞ (ng•h/mL) | t½(h) | CL/F (L/h)
4001 | 983 (53) | 3.3 (35) | 7479 (51) | 9.0 (53) | 68 (50)
8002 | 1816 (43) | 3.0 (39) | 15044 (46) | 8.0 (58) | 66 (51)
1Subjects received 1x400 mg tablet under fasted conditions (N=42)
2Subjects received 2x400 mg tablets under fasted conditions (N=59)

Food Effects

A randomized, two-way, crossover study was conducted in 42 healthy volunteers (31 males, 11 females) administered one 400 mg metaxalone tablet under fasted conditions and following a standard high-fat breakfast. Subjects ranged in age from 18 to 48 years (mean age = 23.5 ± 5.7 years). Compared to fasted conditions, the presence of a high fat meal at the time of drug administration increased Cmax by 177.5% and increased AUC (AUC0-t, AUC∞) by 123.5% and 115.4%, respectively. Time-to-peak concentration (Tmax) was also delayed (4.3 h versus 3.3 h) and terminal half-life was decreased (2.4 h versus 9.0 h) under fed conditions compared to fasted.

In a second food effect study of similar design, two 400 mg metaxalone tablets (800 mg) were administered to healthy volunteers (N=59, 37 males, 22 females), ranging in age from 18 to 50 years (mean age = 25.6± 8.7 years). Compared to fasted conditions, the presence of a high fat meal at the time of drug administration increased Cmax by 193.6% and increased AUC (AUC0-t, AUC∞) by 146.4% and 142.2%, respectively. Time-to-peak concentration (Tmax) was also delayed (4.9 h versus 3.0 h) and terminal half-life was decreased (4.2 h versus 8.0 h) under fed conditions compared to fasted conditions. Similar food effect results were observed in the above study when one metaxalone 800 mg tablet was administered in place of two metaxalone 400 mg tablets. The increase in metaxalone exposure coinciding with a reduction in half-life may be attributed to more complete absorption of metaxalone in the presence of a high fat meal (Figure 1).

Distribution, Metabolism, and Excretion

Although plasma protein binding and absolute bioavailability of metaxalone are not known, the apparent volume of distribution (V/F ~ 800 L) and lipophilicity (log P = 2.42) of metaxalone suggest that the drug is extensively distributed in the tissues. Metaxalone is metabolized by the liver and excreted in the urine as unidentified metabolites. Hepatic Cytochrome P450 enzymes play a role in the metabolism of metaxalone. Specifically, CYP1A2, CYP2D6, CYP2E1, and CYP3A4 and, to a lesser extent, CYP2C8, CYP2C9, and CYP2C19 appear to metabolize metaxalone.

Metaxalone does not significantly inhibit major CYP enzymes such as CYP1A2, CYP2A6, CYP2B6, CYP2C8, CYP2C9, CYP2C19, CYP2D6, CYP2E1, and CYP3A4. Metaxalone does not significantly induce major CYP enzymes such as CYP1A2, CYP2B6, and CYP3A4 in vitro.

Pharmacokinetics in Special Populations

Age: The effects of age on the pharmacokinetics of metaxalone were determined following single administration of two 400 mg tablets (800 mg) under fasted and fed conditions. The results were analyzed separately, as well as in combination with the results from three other studies. Using the combined data, the results indicate that the pharmacokinetics of metaxalone are significantly more affected by age under fasted conditions than under fed conditions, with bioavailability under fasted conditions increasing with age.

The bioavailability of metaxalone under fasted and fed conditions in three groups of healthy volunteers of varying age is shown in Table 2.

Table 2: Mean (%CV) Pharmacokinetic Parameters Following Single Administration of Two 400 mg Metaxalone Tablets (800 mg) under Fasted and Fed Conditions
 | Younger Volunteers | Older Volunteers
Age (years) | 25.6 ± 8.7 | 39.3 ± 10.8 | 71.5 ± 5.0
N | 59 | 21 | 23
Food | Fasted | Fed | Fasted | Fed | Fasted | Fed
Cmax (ng/mL) | 1816; (43) | 3510; (41) | 2719; (46) | 2915; (55) | 3168; (43) | 3680; (59)
Tmax (h) | 3.0; (39) | 4.9; (48) | 3.0; (40) | 8.7; (91) | 2.6; (30) | 6.5; (67)
AUC0-t (ng·h/mL) | 14531; (47) | 20683; (41) | 19836; (40) | 20482; (37) | 23797; (45) | 24340; (48)
AUC∞ (ng·h/mL) | 15045; (46) | 20833; (41) | 20490; (39) | 20815; (37) | 24194; (44) | 24704; (47)

Gender: The effect of gender on the pharmacokinetics of metaxalone was assessed in an open label study, in which 48 healthy adult volunteers (24 males, 24 females) were administered two metaxalone 400 mg tablets (800 mg) under fasted conditions. The bioavailability of metaxalone was significantly higher in females compared to males as evidenced by Cmax (2115 ng/mL versus 1335 ng/mL) and AUC∞ (17884 ng·h/mL versus 10328 ng·h/mL). The mean half-life was 11.1 hours in females and 7.6 hours in males. The apparent volume of distribution of metaxalone was approximately 22% higher in males than in females, but not significantly different when adjusted for body weight. Similar findings were also seen when the previously described combined dataset was used in the analysis.

Hepatic/Renal Insufficiency: The impact of hepatic and renal disease on the pharmacokinetics of metaxalone has not been determined. In the absence of such information, metaxalone tablets should be used with caution in patients with hepatic and/or renal impairment.

INDICATIONS & USAGE SECTION

Metaxalone tablets are indicated as an adjunct to rest, physical therapy, and other measures for the relief of discomforts associated with acute, painful musculoskeletal conditions. The mode of action of this drug has not been clearly identified, but may be related to its sedative properties. Metaxalone does not directly relax tense skeletal muscles in man.

CONTRAINDICATIONS SECTION

Known hypersensitivity to any components of this product.

Known tendency to drug induced, hemolytic, or other anemias.

Significantly impaired renal or hepatic function

WARNINGS SECTION

Metaxalone tablets may enhance the effects of alcohol and other CNS depressants

PRECAUTIONS SECTION

Metaxalone should be administered with great care to patients with pre-existing liver damage. Serial liver function studies should be performed in these patients.

False-positive Benedict's tests, due to an unknown reducing substance, have been noted. A glucose-specific test will differentiate findings.

Taking metaxalone tablets with food may enhance general CNS depression; elderly patients may be especially susceptible to this CNS effect. (See CLINICAL PHARMACOLOGY: Pharmacokinetics and PRECAUTIONS: Information for Patients sections).

Information for Patients

Metaxalone tablets may impair mental and/or physical abilities required for performance of hazardous tasks, such as operating machinery or driving a motor vehicle, especially when used with alcohol or other CNS depressants.

Drug Interactions

The sedative effects of metaxalone tablets and other CNS depressants (e.g., alcohol, benzodiazepines, opiods, trycyclic antidepressants) may be additive. Therefore, caution should be exercised with patients who take more than one of these CNS depressants simultaneoulsy.

Carcinogenesis, Mutagenesis, Impairment of Fertility

The carcinogenic potential of metaxalone has not been determined.

Pregnancy

Reproduction studies in rats have not revealed evidence of impaired fertility or harm to the fetus due to metaxalone. Post marketing experience has not revealed evidence of fetal injury, but such experience cannot exclude the possibility of infrequent or subtle damage to the human fetus. Safe use of metaxalone has not been established with regard to possible adverse effects upon fetal development. Therefore, metaxalone tablets should not be used in women who are or may become pregnant and particularly during early pregnancy unless, in the judgement of the physician, the potential benefits outweigh the possible hazards.

NURSING MOTHERS

It is not known whether this drug is secreted in human milk. As a general rule, nursing should not be undertaken while a patient is on a drug since many drugs are excreted in human milk.

Pediatric Use

Safety and effectiveness in children 12 years of age and below have not been established.

ADVERSE REACTIONS SECTION

The most frequent reactions to metaxalone include:

CNS: drowsiness, dizziness, headache, and nervousness or “irritability”;

Digestive: nausea, vomiting, gastrointestinal upset.

Other adverse reactions are:

Immune System: hypersensitivity reaction, rash with or without pruritus;

Hematologic: leukopenia; hemolytic anemia;

Hepatobiliary: jaundice.

Though rare, anaphylactoid reactions have been reported with metaxalone.

OVERDOSAGE SECTION

Deaths by deliberate or accidental overdose have occurred with metaxalone, particularly in combination with antidepressants, and have been reported with this class of drug in combination with alcohol.

When determining the LD50 in rats and mice, progressive sedation, hypnosis and finally respiratory failure were noted as the dosage increased. In dogs, no LD50 could be determined as the higher doses produced an emetic action in 15 to 30 minutes.

Treatment - Gastric lavage and supportive therapy. Consultation with a regional poison control center is recommended

DOSAGE & ADMINISTRATION SECTION

The recommended dose for adults and children over 12 years of age is one 800 mg tablet three to four times a day.

HOW SUPPLIED SECTION

Metaxalone tablets are available as an 800 mg oval, convex, pink tablet with one side debossed "M" and other side debossed "58/59".

Bottles of 100 NDC 64720-321-10

Bottles of 500 NDC 64720-321-50

Store at Controlled Room Temperature, between 15°C and 30°C (59°F and 86°F).